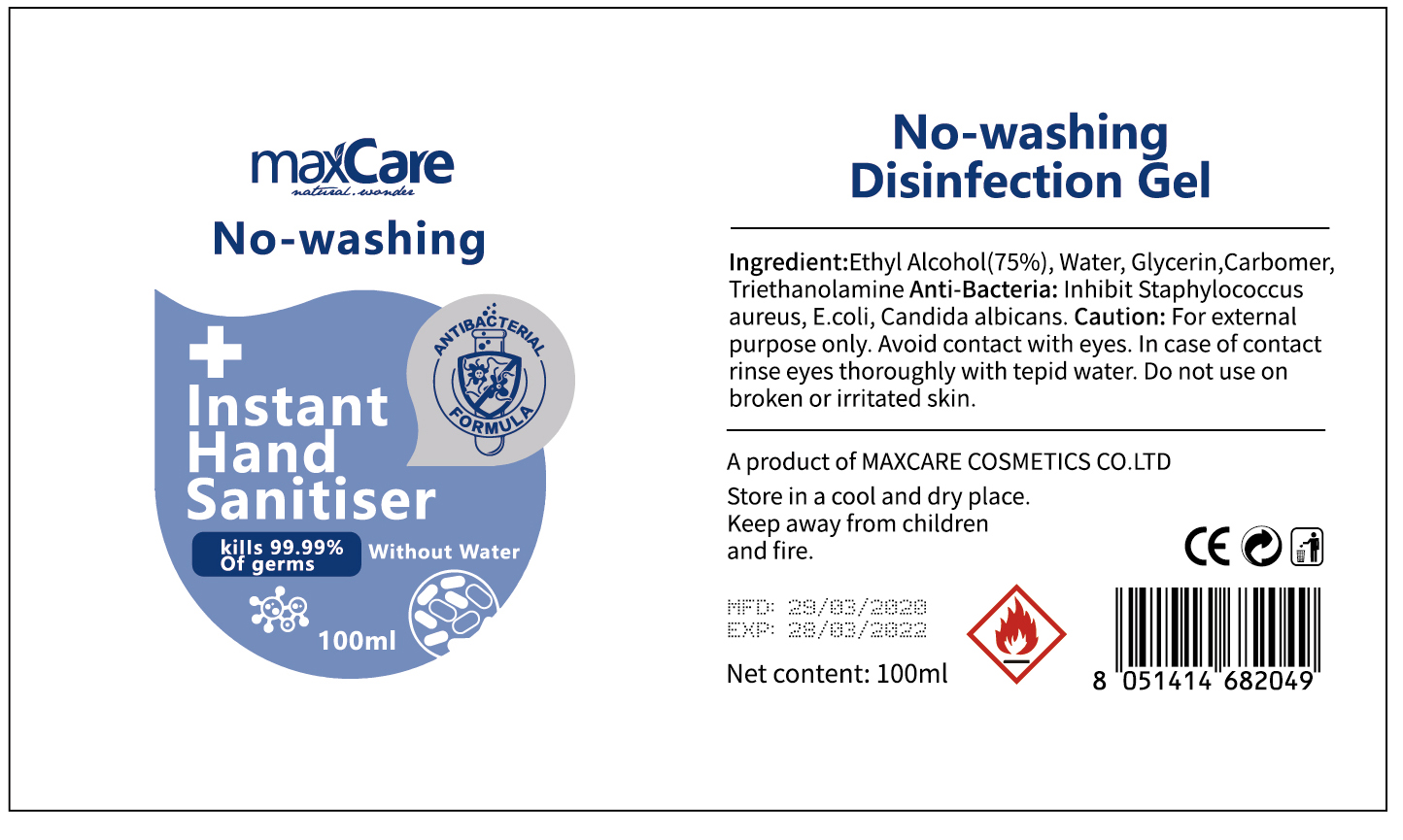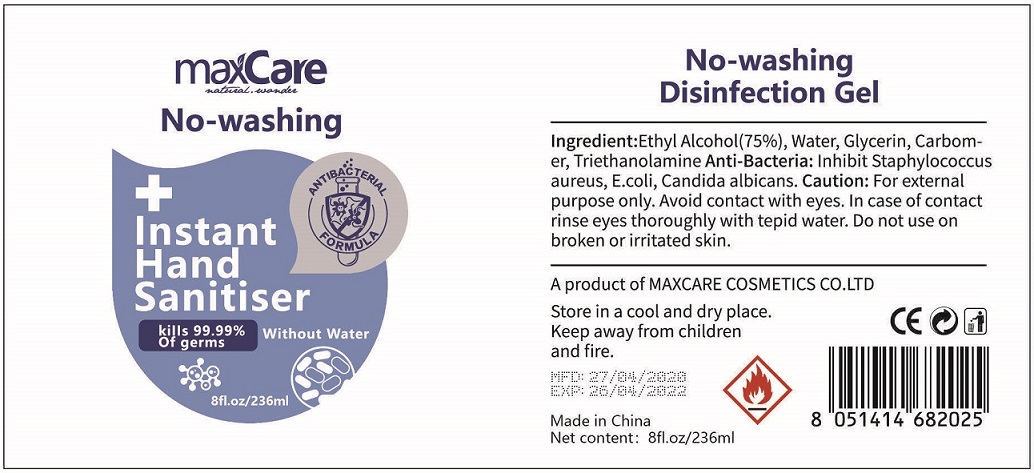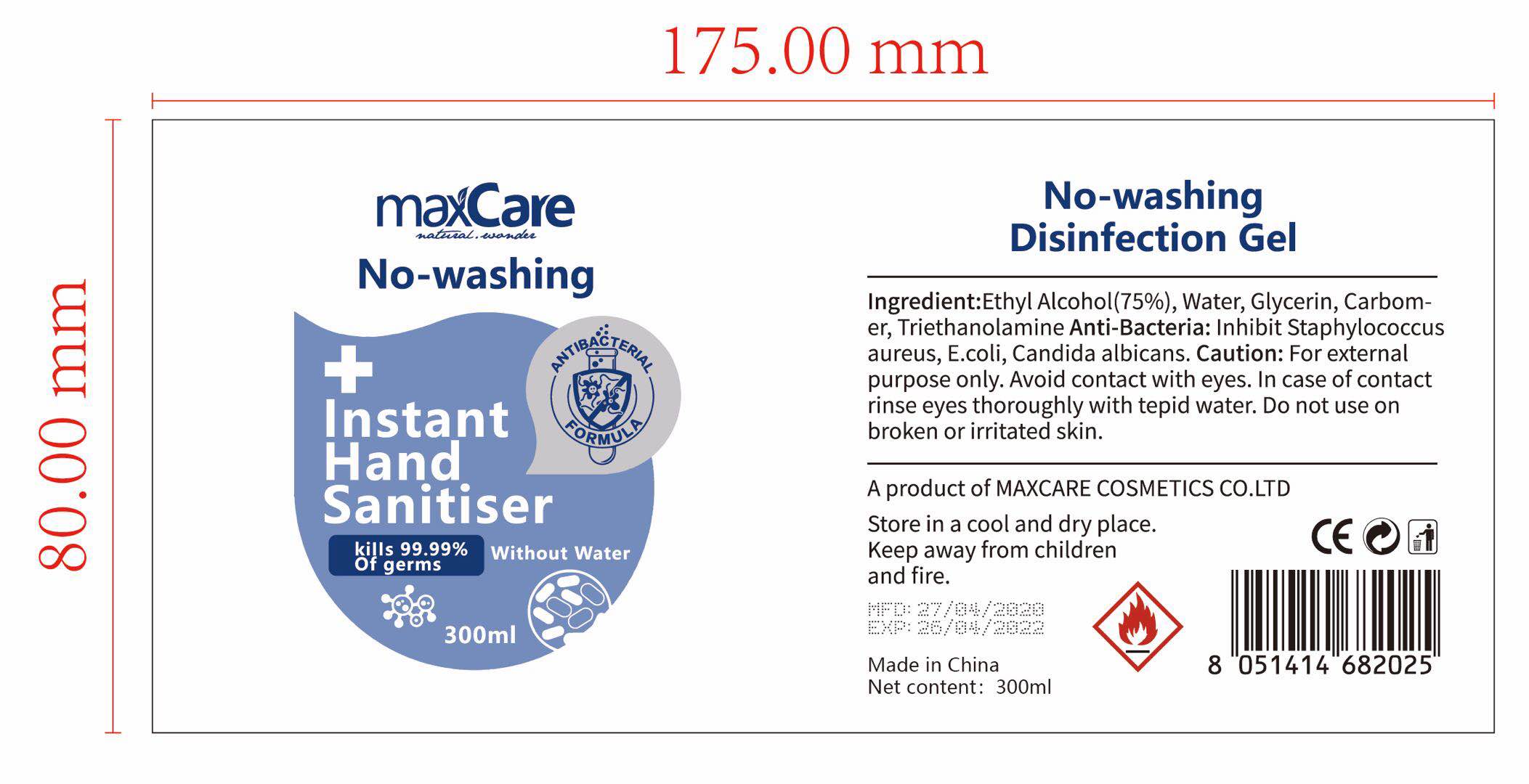 DRUG LABEL: Instant Hand Sanitiser
NDC: 75309-0101 | Form: GEL
Manufacturer: Maxcare (Guangzhou) Cosmetics Co., Ltd.
Category: otc | Type: HUMAN OTC DRUG LABEL
Date: 20200602

ACTIVE INGREDIENTS: ALCOHOL 75 mL/100 mL
INACTIVE INGREDIENTS: GLYCERIN; WATER; CARBOMER 940; TROLAMINE

Maxcare, Sanitizer, 75% Alcohol, Gel, 100mL & 236mL & 300mL

Active Ingredient(s)

Ethyl Alcohol 75% v/v. Purpose: Antiseptic

Purpose

Antiseptic, Hand Sanitizer

Use

Hand Sanitizer to help reduce bacteria that potentially can cause disease. For use when soap and water are not available.

Warnings

Flammable. For external use only. Keep away from heat or flame.

Do not use

- on children less than 2 months of age
- on open skin wounds
- in the eyes. in case of contact, rinse eyes thoroughly with water

When using this product keep out of eyes, ears, and mouth.

In case of contact with eyes, rinse eyes thoroughly with water.

Stop use and ask a doctor if irritation and redness develop and persist for more than 72 hours.

Keep out of reach of children. If swallowed, get medical help or contact a Poison Control Center right away.

Directions

- wet hands thoroughly with product briskly rub hands together until dry.
- children under 6 years of age should be supervised by an adult when using.

Other information

- Do not store above 105℉ (40.6℃)
- May discolor some fabrics
- Harmful to wood finishes and plastics

Inactive ingredients

Water, Glycerin, Carbomer, Triethanolamine.